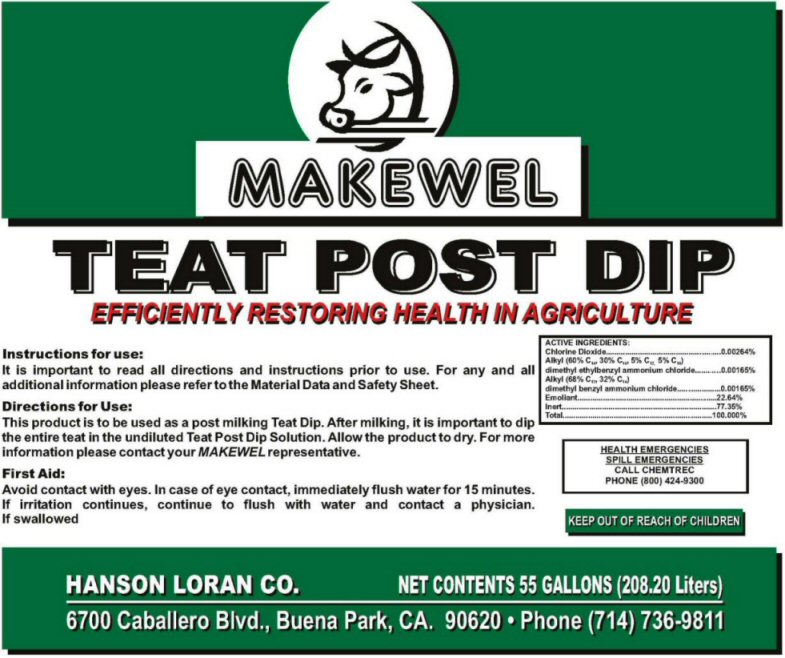 DRUG LABEL: Makewel Teat Post Dip
NDC: 76036-001 | Form: LIQUID
Manufacturer: Southren California Distributors, Inc. dba Hanson Loran
Category: animal | Type: OTC ANIMAL DRUG LABEL
Date: 20110221

ACTIVE INGREDIENTS: CHLORINE DIOXIDE 0.00264 L/1 L; N-ALKYL ETHYLBENZYL DIMETHYL AMMONIUM CHLORIDE (C12-C14) 0.00165 L/1 L; BENZALKONIUM CHLORIDE 0.00165 L/1 L
INACTIVE INGREDIENTS: WATER; GLYCERIN

Ingredients

Chlorine Dioxide - 0.00264% Alkyl (60% C14, 30% C16, 5% C12, 5% C18) dimethyl ethylbenzyl ammonium chloride - 0.00165% Alkyl (68% C12, 32% C14) dimethyl benzyl ammonium chloride 0.00165% Emmoliant - 22.65%, Inert - 77.35%, Total - 100%

Teat Dip Label

Makewel Teat Post Dip Efficiently Restoring Health In Agriculture
Instructions For Use
It is important to read all directions and instructions prior to use. For any and all additional information please refer to the Material Data and Safety Sheet.
Directions For Use
This product is to be used as a post milking Teat Dip. After Milking, it is important to dip the entire teat in the undiluted Teat Post Dip Solution. Allow the product to dry. For more information please contact your MAKEWEL representative.
First Aid
Avoid contact with eyes. In case of eye contact, immediately flush water for 15 minutes. If irritation continues, continue to flush with water and contact a physician.
Health Emergencies, Spill Emergencies call Chemtrec Phone (800) 424-9300
Keep Out Of Reach Of Children Net Contents:_____________
Hanson Loran Co. 6700 Caballero Blvd., Buena Park, CA. 90620 Phone (714) 736-9811